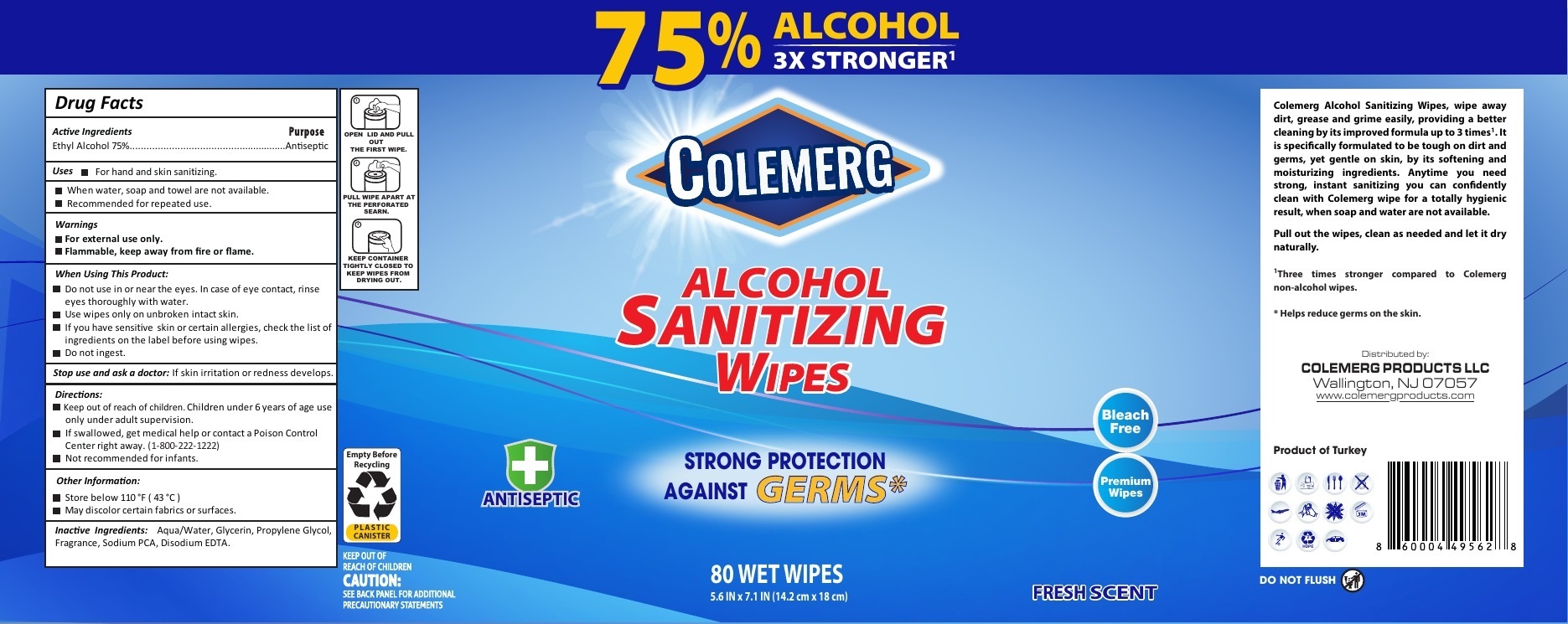 DRUG LABEL: Colemerg Sanitizing Wipes
NDC: 80171-003 | Form: CLOTH
Manufacturer: COLEMERG PRODUCTS LLC
Category: otc | Type: HUMAN OTC DRUG LABEL
Date: 20210129

ACTIVE INGREDIENTS: ALCOHOL 0.75 mL/1 mL
INACTIVE INGREDIENTS: WATER; GLYCERIN; PROPYLENE GLYCOL; SODIUM PYRROLIDONE CARBOXYLATE; EDETATE DISODIUM ANHYDROUS

Colemerg Sanitizing Wipes

Active Ingredients

Ethyl Alcohol 75%

Purpose

Antiseptic

Uses

- For hand and skin sanitizing.
- When water, soap and towel are not available.
- Recommended for repeated use.

WARNINGS

- For external use only.
- Flammable, keep away from fire or flame.

When Using This Product:

- Do not use in or near the eyes. In case of eye contact, rinse eyes thoroughly with water.
- Use wipes only on unbroken intact skin.
- If you have sensitive skin or certain allergies, check the list of ingredients on the label before using wipes.
- Do not ingest.

Stop use and ask a doctor:

If skin irritation or redness develops.

Keep out of reach of children.

- Children under 6 years of age use only under adult supervision.
- If swallowed, get medical help or contact a Poison Control Center right away. (1-800-222-1222)

Directions:

Not recommended for infants.

Other Information:

- Store below 110 °F (43 °C)
- May discolor certain fabrics or surfaces.

Inactive Ingredients:

Aqua/Water, Glycerin, Propylene Glycol, Fragrance, Sodium PCA, Disodium EDTA.